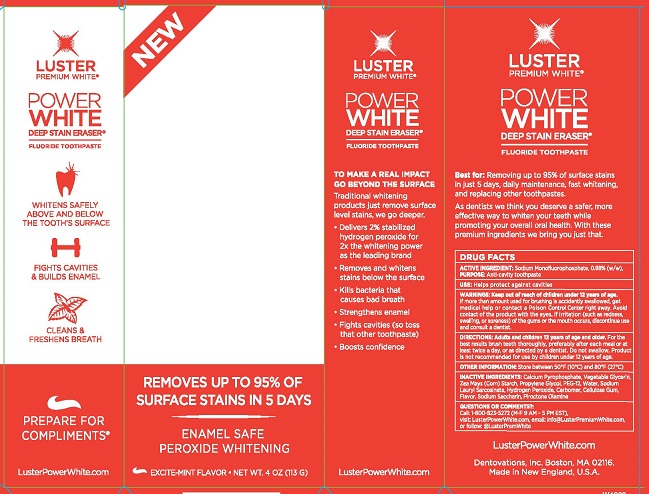 DRUG LABEL: LUSTER POWER WHITE
NDC: 57353-106 | Form: GEL, DENTIFRICE
Manufacturer: DENTOVATIONS INC
Category: otc | Type: HUMAN OTC DRUG LABEL
Date: 20190226

ACTIVE INGREDIENTS: SODIUM MONOFLUOROPHOSPHATE 0.88 g/100 g
INACTIVE INGREDIENTS: GLYCERIN; CALCIUM PYROPHOSPHATE; STARCH, CORN; PROPYLENE GLYCOL; POLYETHYLENE GLYCOL 600; WATER; HYDROGEN PEROXIDE; SODIUM LAUROYL SARCOSINATE; CARBOXYMETHYLCELLULOSE SODIUM, UNSPECIFIED FORM; CARBOMER 934; SACCHARIN SODIUM; PIROCTONE OLAMINE

Luster Power White

Drug Facts

ACTIVE INGREDIENT: Sodium Monofluorophosphate 0.88% (w/w)

PURPOSE: Anti-cavity toothpaste

INDICATIONS AND USAGE

USE: Helps protect against cavities

WARNINGS:

Keep out of reach of children under 12 years of age. If more than used for brushing is accidently swallowed, get medical help or contact a Poison Control Center right away. Avoid contact of the product with the eyes. If irritation (such as redness, swelling or soreness) of the gums or the mouth occurs, discontinue use and consult a dentist.

DOSAGE AND ADMINISTRATION

DIRECTIONS: Adults and children 12 years of age and older. For the best results brush teeth thoroughly, preferably after each meal or least twice a day, or as directed by a dentist. Do not swallow. Product is not recommended for use by children under 12 years of age.

OTHER INFORMATION: Store between 50°F (10°C) and 80°F (27°C)

INACTIVE INGREDIENT

INACTIVE INGREDIENTS: Calcium Pyrophosphate, Vegetable Glycerin, Zea Mays (Corn) Starch, Propylene Glycol, PEG-12, Water, Sodium Lauroyl Sarcosinate, Hydrogen Peroxide, Carbomer, Cellulose Gum, Flavor, Sodium Saccharin, Piroctone Olamine

QUESTIONS OR COMMENTS?

Call 1-800-823-5727 (M-F 9 A.M. - 5 P.M. EST)

visit LusterPowerWhite.com, email: info@lusterpremiumwhite.com or follow: @LusterPremWhite

Dentovations, Inc.

Boston, MA 02116

Made in New England, U.S.A.

PACKAGE LABEL

LUSTER PREMIUM WHITE

POWER WHITE

DEEP STAIN ERASER

FLUORIDE TOOTHPASTE

REMOVES UP TO 95% OF SURFACE STAINS IN 5 DAYS

ENAMEL SAFE

PEROXIDE WHITENING

EXCITE-MINT FLAVOR

NET WT. 4 OZ (113 G)